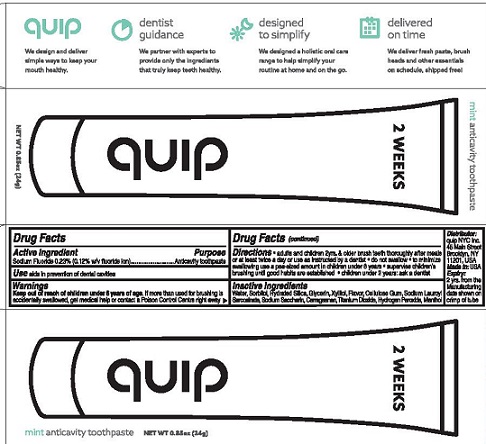 DRUG LABEL: Quip
NDC: 69261-002 | Form: PASTE, DENTIFRICE
Manufacturer: Quip NYC Inc.
Category: otc | Type: HUMAN OTC DRUG LABEL
Date: 20250130

ACTIVE INGREDIENTS: SODIUM FLUORIDE 0.23 g/100 g
INACTIVE INGREDIENTS: CARRAGEENAN; CARBOXYMETHYLCELLULOSE SODIUM, UNSPECIFIED FORM; GLYCERIN; TITANIUM DIOXIDE; SODIUM LAUROYL SARCOSINATE; SORBITOL; WATER; HYDRATED SILICA; SACCHARIN SODIUM; XYLITOL; HYDROGEN PEROXIDE; MENTHOL

Quip Anticavity Toothpaste

Drug Facts

Active ingredient

Sodium fluoride 0.23% (0.12% w/v fluoride ion)

Purpose

Anticavity toothpaste

Use

aids in prevention of dental cavities

Warnings

Keep out of reach of children under 6 years of age.If more than used for brushing is accidentally swallowed, get medical help or contact a Poison Control Centre right away.

Directions

- adults and children 2yrs. & older: brush teeth thoroughly after meals or at least twice a day or use as instructed by a dentist
- do not swallow
- to minimize swallowing use a pea-sized amount in children under 6 years
- supervise children's brushing until good habits are established
- children under 2 years: ask a dentist

Inactive ingredients

Water, Sorbitol, Hydrated Silica, Glycerin, Xylitol, Flavor, Cellulose Gum, Sodium Lauroyl Sarcosinate, Sodium Saccharin, Carrageenan, Titanium Dioxide, Hydrogen Peroxide, Menthol

Info

Distributor:quip NYC Inc., 45 Main Street, Brooklyn, NY 11201, USA

Made in:USA

Expiry:2 years from the Manufacturing date shown on crimp of toothpaste tube

Questions?help@getquip.com

quip

We design and deliver simple ways to keep your mouth healthy.

dentist guidance

We partner with experts to provide only the ingredients that truly keep teeth healthy.

designed to simplify

We designed a holistic oral care range to help simplify your routine at home or on the go.

delivered on time

We deliver fresh paste, brush heads and other essentials on schedule, shipped free!

PACKAGE LABEL

2 WEEKS

QUIP

mint anticavity toothpaste

NET WT 0.85oz (24g)